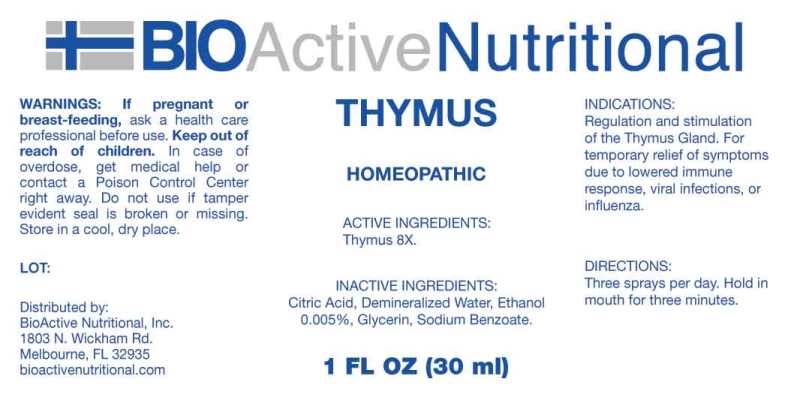 DRUG LABEL: THYMUS
NDC: 43857-0194 | Form: LIQUID
Manufacturer: BioActive Nutrional, Inc.
Category: homeopathic | Type: HUMAN OTC DRUG LABEL
Date: 20241018

ACTIVE INGREDIENTS: SUS SCROFA THYMUS 8 [hp_X]/1 mL
INACTIVE INGREDIENTS: CITRIC ACID MONOHYDRATE; GLYCERIN; SODIUM BENZOATE; WATER; ALCOHOL

DRUG FACTS:

ACTIVE INGREDIENTS:

Thymus (Suis) 8X.

INDICATIONS:

Regulation and stimulation of the Thymus Gland. For temporary relief of symptoms due to lowered immune response, viral infections, or influenza.

WARNINGS:

If pregnant or breast-feeding, ask a health care professional before use.

Keep out of reach of children. In case of overdose, get medical help or contact a Poison Control Center right away.

Do not use if tamper evident seal is broken or missing.

Store in a cool, dry place.

Keep out of reach of children. In case of overdose, get medical help or contact a Poison Control Center right away.

DIRECTIONS:

Three sprays per day. Hold in mouth for three minutes.

INDICATIONS:

Regulation and stimulation of the Thymus Gland. For temporary relief of symptoms due to lowered immune response, viral infections, or influenza.

INACTIVE INGREDIENTS:

Citric Acid, Demineralized Water, Ethanol 0.005%, Glycerin, Sodium Benzoate.

QUESTIONS:

Distributed by:

Bio Active Nutritional, Inc.

Melbourne, FL 32935

bioactivenutritional.com

PACKAGE LABEL DISPLAY:

BIOActive Nutritional

THYMUS

HOMEOPATHIC

1 FL OZ (30 ml)